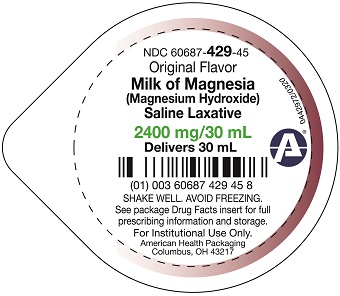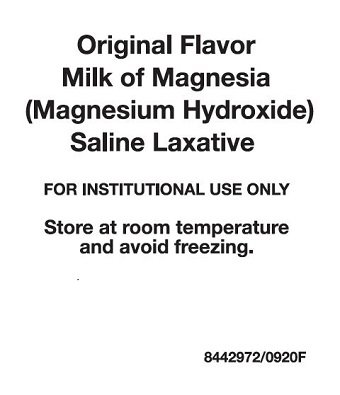 DRUG LABEL: MILK OF MAGNESIA ORIGINAL
NDC: 60687-429 | Form: LIQUID
Manufacturer: American Health Packaging
Category: otc | Type: HUMAN OTC DRUG LABEL
Date: 20241021

ACTIVE INGREDIENTS: MAGNESIUM HYDROXIDE 1200 mg/15 mL
INACTIVE INGREDIENTS: WATER; SODIUM HYPOCHLORITE

Original Flavor Milk of Magnesia
(Magnesium Hydroxide)
Saline Laxative
8442972/0820F

Active ingredient (in each 30 mL cup)

Magnesium hydroxide 2400 mg

Purpose

Saline laxative

Uses

- relieves occasional constipation (irregularity)
- usually produces bowel movement in 1/2 to 6 hours

Warnings

Ask a doctor before use if you have

- kidney disease
- a magnesium-restricted diet
- stomach pain, nausea, or vomiting
- a sudden change in bowel habits that lasts over 14 days

Ask a doctor or pharmacist before use if you are
taking a prescription drug.

This product may interact with certain prescription drugs.

Stop use and ask a doctor if

- you have rectal bleeding or no bowel movement after using this product. These could be signs of a serious condition.
- you need to use a laxative for more than 1 week

If pregnant or breast-feeding,
ask a health professional before use.

Keep out of reach of children.
In case of overdose, get medical help or contact a Poison Control Center right away.

Directions

- shake well before use
- do not exceed the maximum recommended daily dose in a 24 hour period
- dose may be taken once a day preferably at bedtime, in divided doses, or as directed by a doctor
- drink a full glass (8 oz) of liquid with each dose

adults and children 12 years and older | 1 unit dose cup (30 mL) to 2 unit dose cups (60 mL)
children 6 to 11 years | ½ unit dose cup (15 mL) to 1 unit dose cup (30 mL)
children under 6 years | ask a doctor

Other information

- each 30 mL cup contains: magnesium 1000 mg
- store at room temperature and avoid freezing
- DO NOT USE IF SEAL IS BROKEN
- This drug product is supplied in 30 ml unit dose cups as:
  100 cups (10 x 10) ND 60687-429-76

Inactive ingredients

purified water, sodium hypochlorite

PACKAGING INFORMATION

American Health Packaging unit dose cups (see Other Information section) contain drug product from Geri-Care Pharmaceuticals as follows:
(2400 mg per 30 mL / 100 UD) NDC 60687-429-76 packaged from NDC 57896-649

Distributed by:
American Health Packaging
Columbus, OH 43217

8442972/0920F

Principal Display Panel – Tray

Original Flavor
Milk of Magnesia
(Magnesium Hydroxide)
Saline Laxative

FOR INSTITUTIONAL USE ONLY

Store at room temperature
and avoid freezing.

8442972/0920F

Principal Display Panel – Cup

NDC 60687- 429-45

Original Flavor
Milk of Magnesia
(Magnesium Hydroxide)
Saline Laxative

2400 mg/30 mL
Delivers 30 mL

SHAKE WELL. AVOID FREEZING.

See package Drug Facts insert for full
prescribing information and storage.

For Institutional Use Only

American Health Packaging
Columbus, OH 43217

0442972/0320